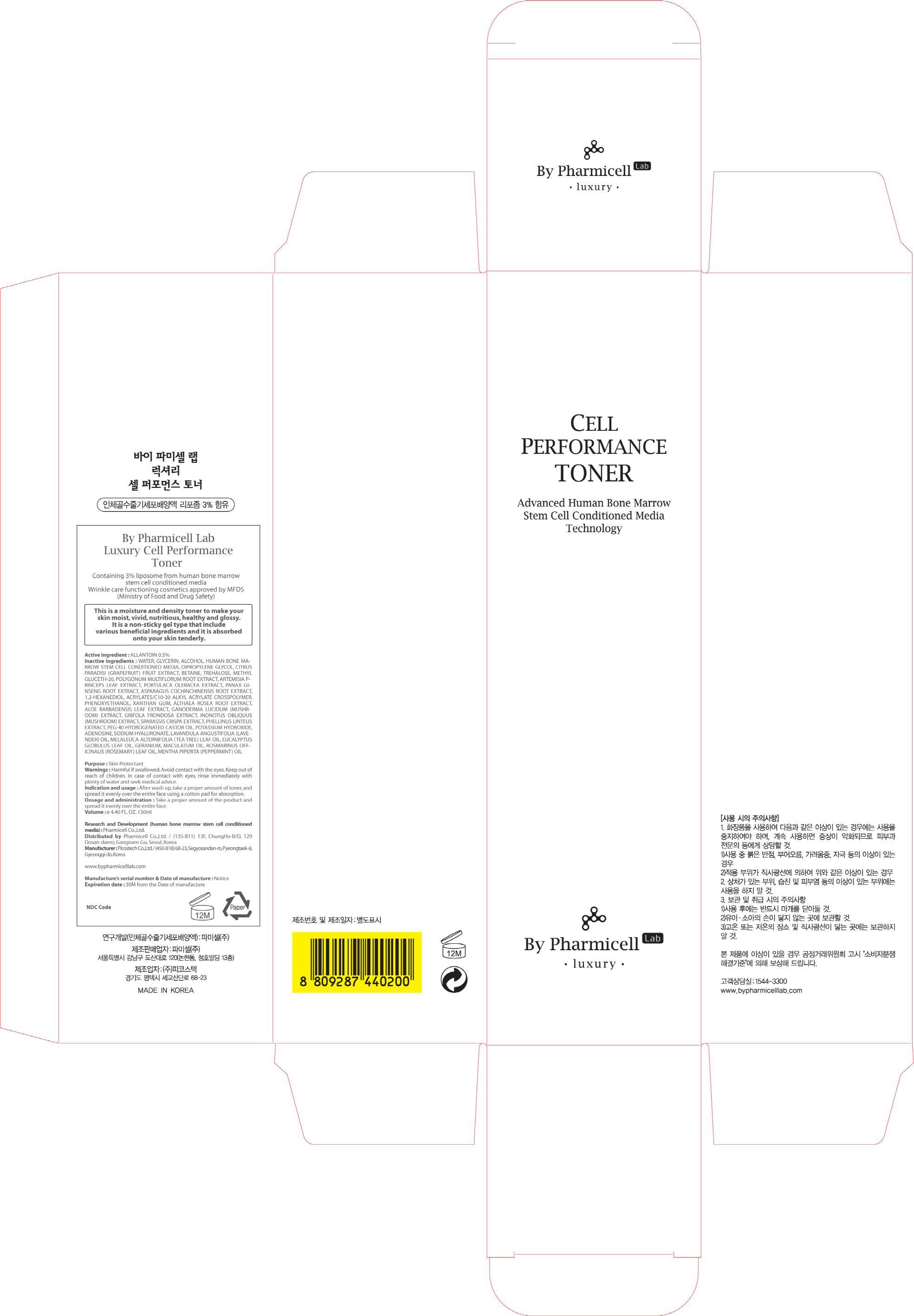 DRUG LABEL: Luxury Cell Performance Toner
NDC: 60949-120 | Form: CREAM
Manufacturer: Pharmicell Co., Ltd.
Category: otc | Type: HUMAN OTC DRUG LABEL
Date: 20140922

ACTIVE INGREDIENTS: ALLANTOIN 0.65 mg/130 mL
INACTIVE INGREDIENTS: WATER; GLYCERIN

ACTIVE INGREDIENT

Active ingredient : ALLANTOIN 0.5%

INACTIVE INGREDIENT

Inactive ingredients : WATER, GLYCERIN, ALCOHOL, HUMAN BONE MARROW STEM CELL CONDITIONED MEDIA, DIPROPYLENE GLYCOL, CITRUS PARADISI (GRAPEFRUIT) FRUIT EXTRACT, BETAINE, TREHALOSE, METHYL GLUCETH-20, POLYGONUM MULTIFLORUM ROOT EXTRACT, ARTEMISIA PRINCEPS LEAF EXTRACT, PORTULACA OLERACEA EXTRACT, PANAX GINSENG ROOT EXTRACT, ASPARAGUS COCHINCHINENSIS ROOT EXTRACT, 1,2-HEXANEDIOL, ACRYLATES/C10-30 ALKYL ACRYLATE CROSSPOLYMER, PHENOXYETHANOL, XANTHAN GUM, ALTHAEA ROSEA ROOT EXTRACT, ALOE BARBADENSIS LEAF EXTRACT, GANODERMA LUCIDUM (MUSHROOM) EXTRACT, GRIFOLA FRONDOSA EXTRACT, INONOTUS OBLIQUUS (MUSHROOM) EXTRACT, SPARASSIS CRISPA EXTRACT, PHELLINUS LINTEUS EXTRACT, PEG-40 HYDROGENATED CASTOR OIL, POTASSIUM HYDROXIDE, ADENOSINE, SODIUM HYALURONATE, LAVANDULA ANGUSTIFOLIA (LAVENDER) OIL, MELALEUCA ALTERNIFOLIA (TEA TREE) LEAF OIL, EUCALYPTUS GLOBULUS LEAF OIL, GERANIUM, MACULATUM OIL, ROSMARINUS OFFICINALIS (ROSEMARY) LEAF OIL, MENTHA PIPERITA (PEPPERMINT) OIL

PURPOSE

Purpose : Skin Protectant

WARNINGS

Warnings : Harmful if swallowed. Avoid contact with the eyes. Keep out of reach of children. In case of contact with eyes, rinse immediately with plenty of water and seek medical advice.

KEEP OUT OF REACH OF CHILDREN

INDICATIONS & USAGE

Indication and usage : After wash up, take a proper amount of toner, and spread it evenly over the entire face using a cotton pad for absorption.

DOSAGE & ADMINISTRATION

Dosage and administration : Take a proper amount of the product and spread it evenly over the entire face.